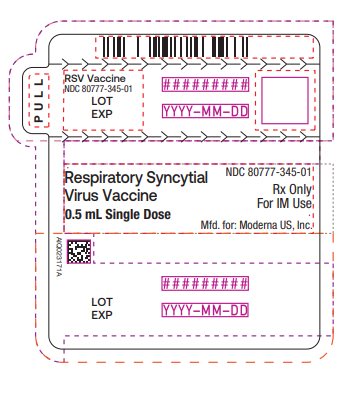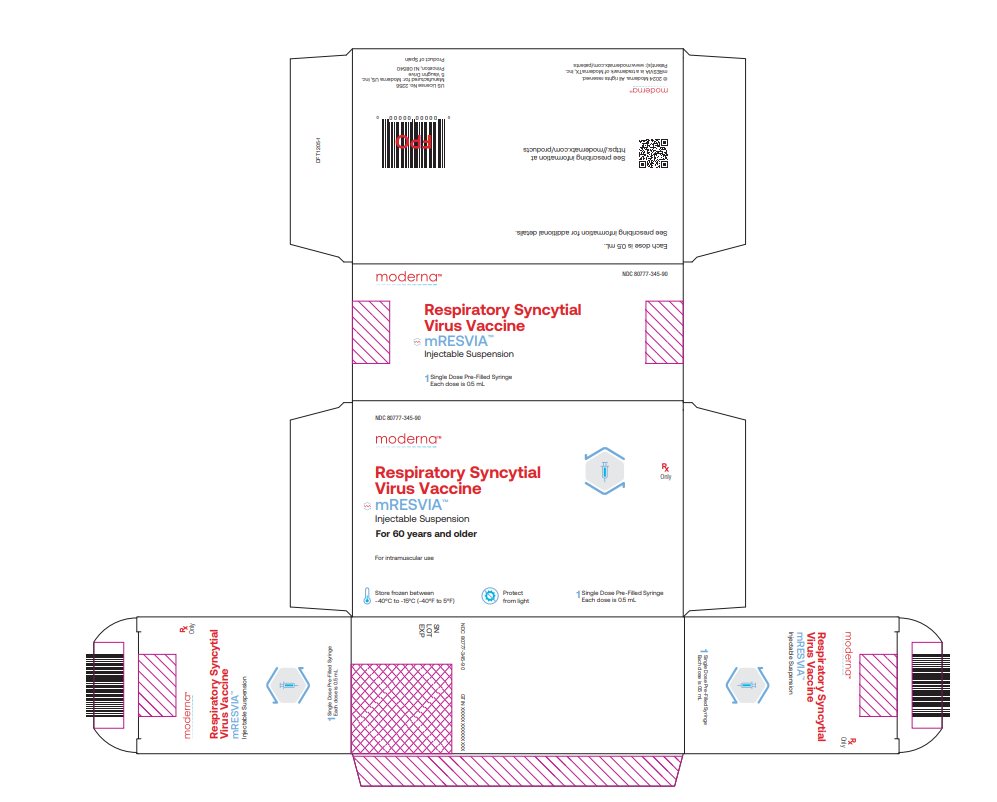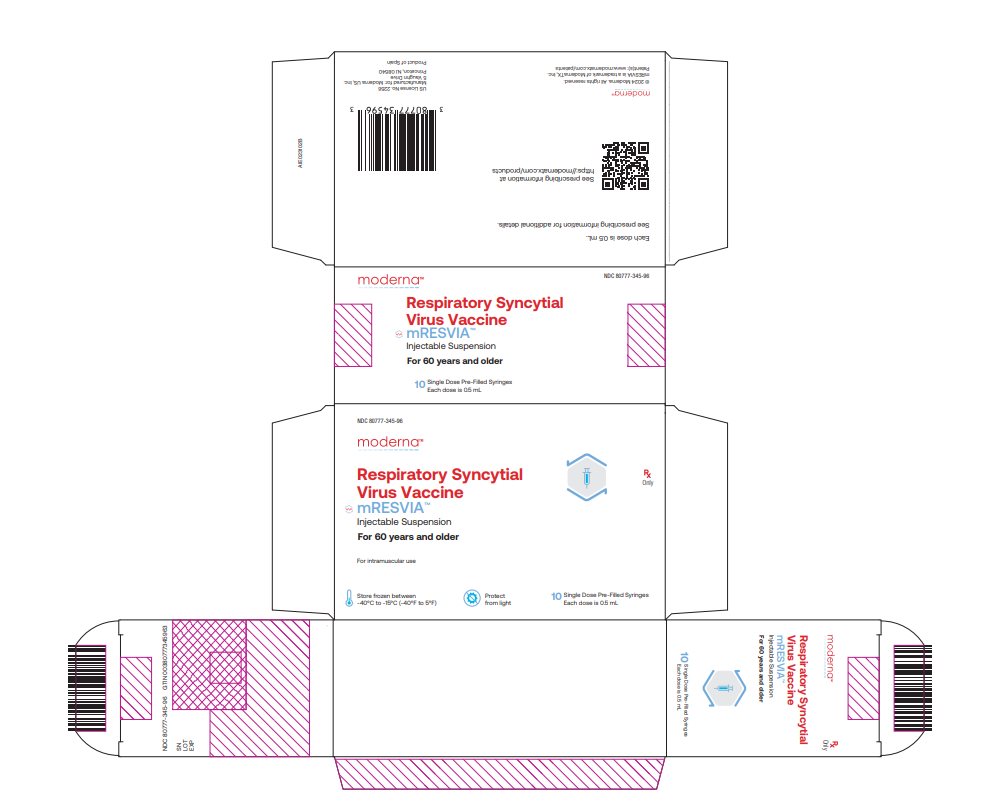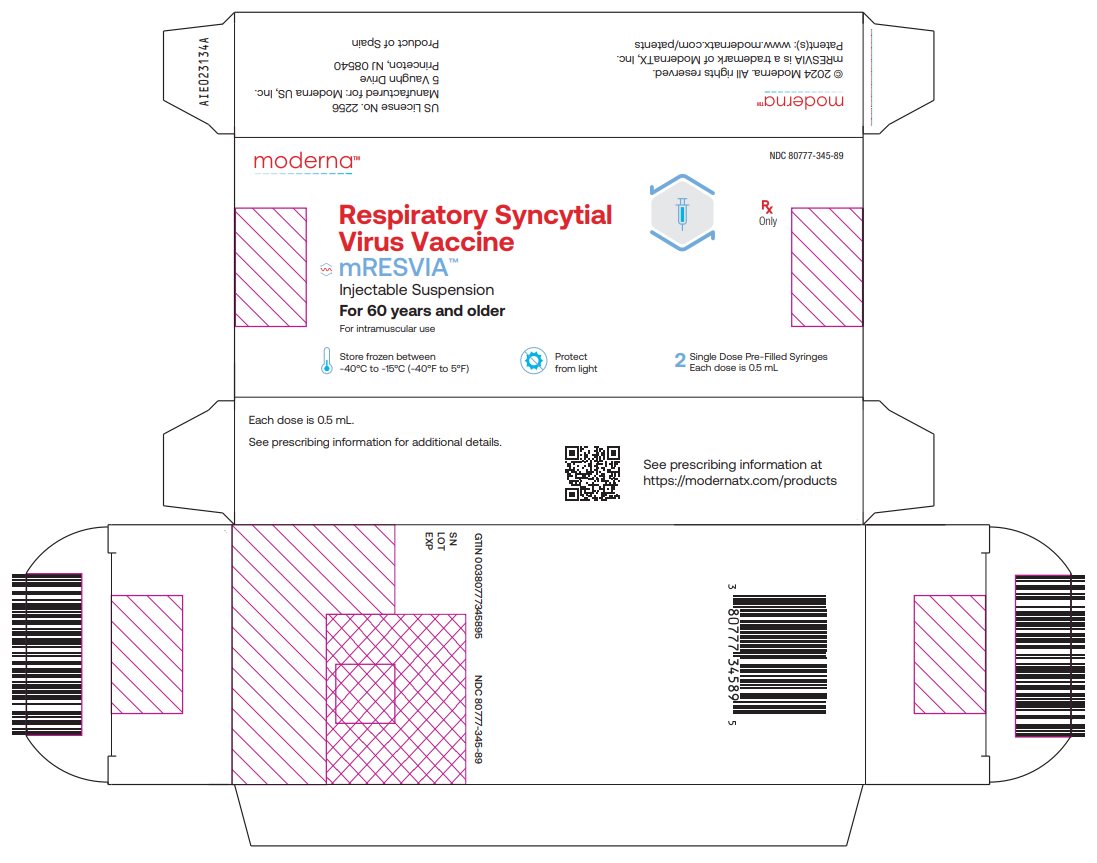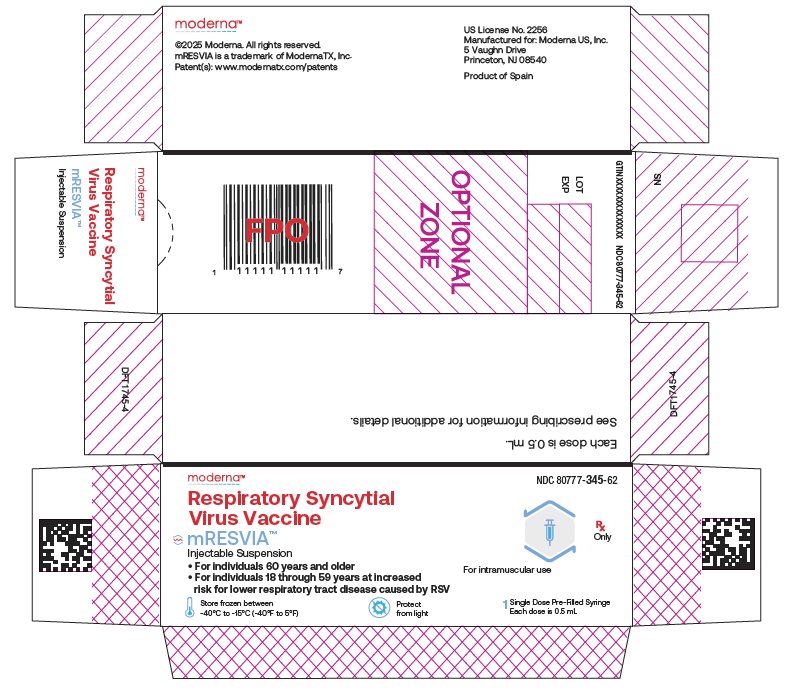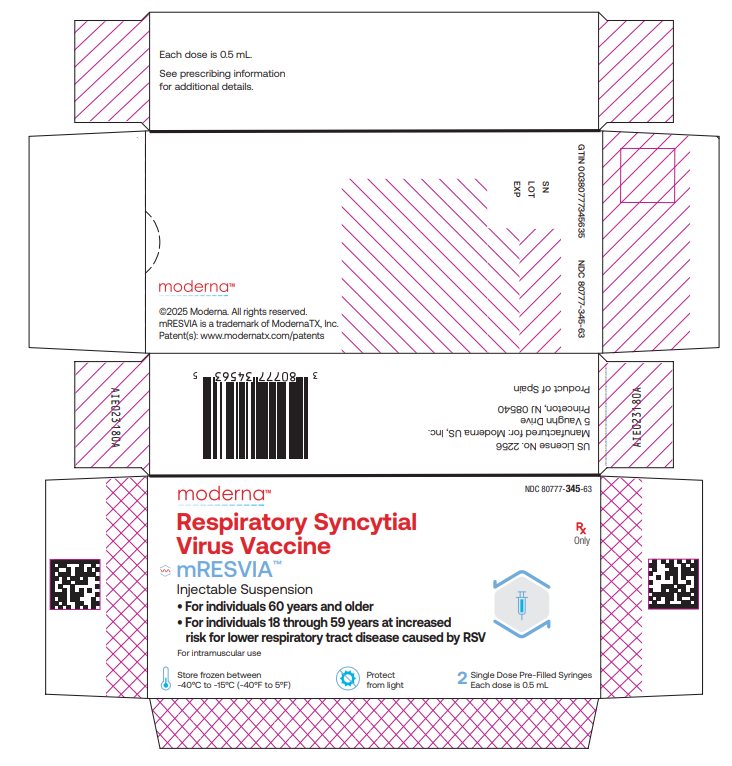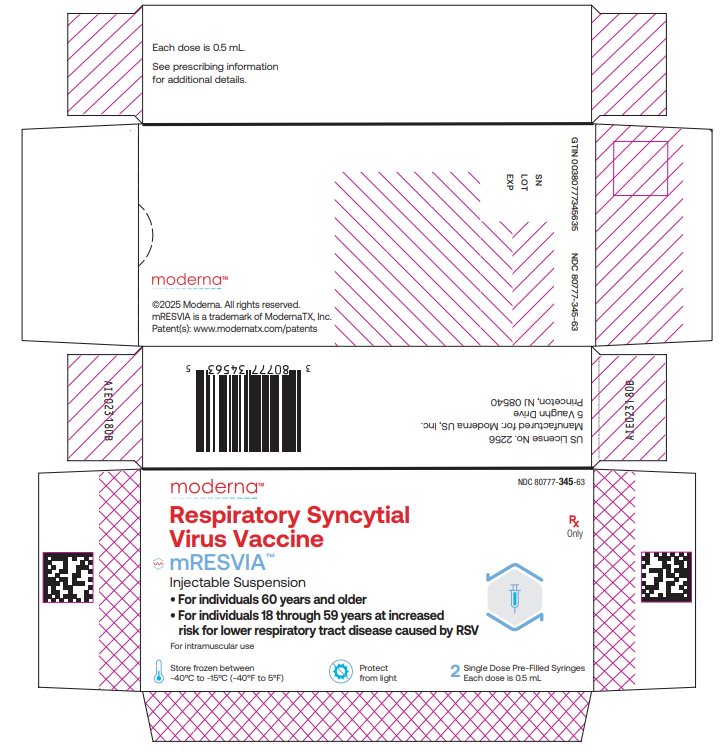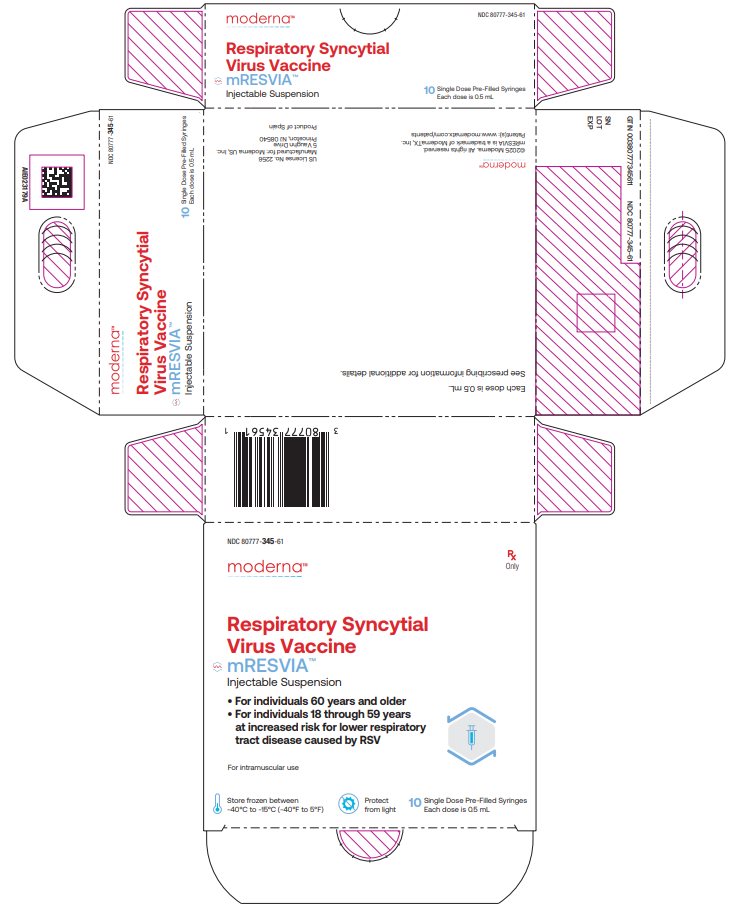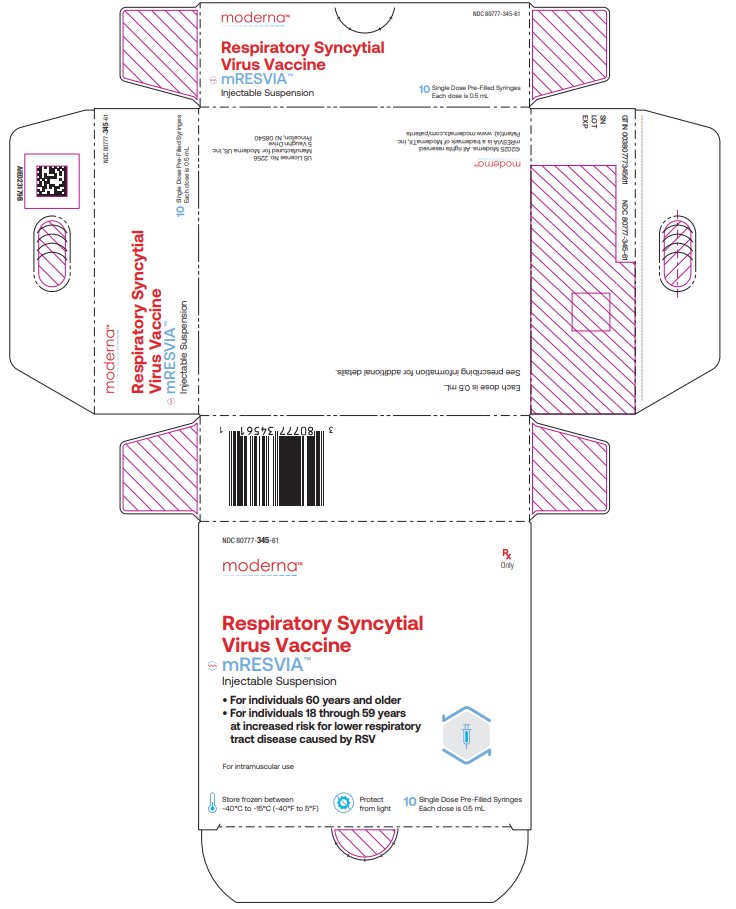 DRUG LABEL: mRESVIA
NDC: 80777-345 | Form: SUSPENSION
Manufacturer: Moderna US, INC.
Category: other | Type: VACCINE LABEL
Date: 20250612

ACTIVE INGREDIENTS: RNA-100-AR02 50 ug/0.5 mL
INACTIVE INGREDIENTS: 1,2-DIMYRISTOYL-RAC-GLYCERO-3-METHOXYPOLYETHYLENE GLYCOL 2000; 1,2-DISTEAROYL-SN-GLYCERO-3-PHOSPHOCHOLINE; ACETIC ACID; CHOLESTEROL; SM-102; SODIUM ACETATE; SUCROSE; TROMETHAMINE; TROMETHAMINE HYDROCHLORIDE; WATER

HIGHLIGHTS OF PRESCRIBING INFORMATION

These highlights do not include all the information needed to use MRESVIA safely and effectively. See full prescribing information for MRESVIA.
MRESVIATM (Respiratory Syncytial Virus Vaccine) injectable suspension, for intramuscular use
Initial U.S. Approval: 2024

RECENT MAJOR CHANGES

• Indications and Usage (1)

• Dosage and Administration (2.2)

06/2025

12/2024

1 INDICATIONS AND USAGE

MRESVIATM is a vaccine indicated for active immunization for the prevention of lower respiratory tract disease (LRTD) caused by respiratory syncytial virus (RSV) in

• individuals 60 years of age and older. (1)

• individuals 18 through 59 years of age who are at increased risk for LRTD caused by RSV. (1)

2 DOSAGE AND ADMINISTRATION

For intramuscular use.

Administer a single dose (0.5 mL). (2.1)

3 DOSAGE FORMS AND STRENGTHS

Injectable suspension. A single dose is 0.5 mL. (3)

4 CONTRAINDICATIONS

History of severe allergic reaction (e.g., anaphylaxis) to any component of MRESVIA. (4)

6 ADVERSE REACTIONS

The most commonly reported (≥10%) adverse reactions in individuals 60 years and older were injection-site pain (55.9%), fatigue (30.8%), headache (26.7%), myalgia (25.6%), arthralgia (21.7%), axillary (underarm) swelling or tenderness (15.2%), and chills (11.6%). (6.1)

The most commonly reported (≥10%) adverse reactions in individuals 18 through 59 years who are at increased risk for LRTD caused by RSV were injection site pain (73.9%), fatigue (36.9%), headache (33.3%), myalgia (28.9%), arthralgia (22.7%), chills (19.9%), axillary (underarm) swelling or tenderness (17.1%), and nausea/vomiting (10.8%). (6.1)

To report SUSPECTED ADVERSE REACTIONS, contact ModernaTX, Inc. at 1-866-663-3762 or VAERS at 1-800-822-7967 or www.vaers.hhs.gov.

FULL PRESCRIBING INFORMATION

1 INDICATIONS AND USAGE

MRESVIA is indicated for active immunization for the prevention of lower respiratory tract disease (LRTD) caused by respiratory syncytial virus (RSV) in

- individuals 60 years of age and older.
- individuals 18 through 59 years of age who are at increased risk for LRTD caused by RSV.

2 DOSAGE AND ADMINISTRATION

2.1 Dose and Schedule

Administer a single dose (0.5 mL) of MRESVIA as an intramuscular injection.

2.2 Preparation for Administration

MRESVIA is supplied as a pre-filled syringe that contains a frozen suspension that must be thawed prior to administration.

Thaw each syringe before use, either in the refrigerator or at room temperature, following the instructions in Table 1.

Table 1: Thawing Conditions and Times
Configuration | Thaw in Refrigerator | Thaw at Room Temperature
Carton of 1 pre-filled syringe | Thaw between 2°C to 8°C (36°F to 46°F) for 100 minutes. | Thaw between 15°C to 25°C (59°F to 77°F) for 40 minutes.
Carton of 2 pre‑filled syringes | Thaw between 2°C to 8°C (36°F to 46°F) for 100 minutes. | Thaw between 15°C to 25°C (59°F to 77°F) for 40 minutes.
Carton of 10 pre-filled syringes | Thaw between 2°C to 8°C (36°F to 46°F) for 160 minutes. | Thaw between 15°C to 25°C (59°F to 77°F) for 80 minutes.
One syringe (removed from carton) | Thaw between 2°C to 8°C (36°F to 46°F) for 100 minutes. | Thaw between 15°C to 25°C (59°F to 77°F) for 40 minutes.

- After thawing, do not refreeze.
- Syringes should not be returned to the refrigerator after standing at room temperature.
- Pre-filled syringes may be stored at 8°C to 25°C (46°F to 77°F) for a total of 24 hours after removal from refrigerated conditions. Discard the thawed pre-filled syringe if not used within this time.
- Do not shake.
- Parenteral drug products should be inspected visually for particulate matter and discoloration prior to administration, whenever solution and container permit.
- MRESVIA is a white to off-white suspension that may contain visible white or translucent product-related particulates. Do not administer if the vaccine is discolored or contains other particulate matter.

2.3 Administration

Administer MRESVIA intramuscularly.

3 DOSAGE FORMS AND STRENGTHS

MRESVIA is an injectable suspension. A single dose is 0.5 mL.

4 CONTRAINDICATIONS

Do not administer MRESVIA to individuals with a history of a severe allergic reaction (e.g., anaphylaxis) to any component of MRESVIA [see Description (11)].

5 WARNINGS AND PRECAUTIONS

5.1 Management of Acute Allergic Reactions

Appropriate medical treatment must be immediately available to manage potential anaphylactic reactions following administration of MRESVIA.

5.2 Syncope

Syncope (fainting) may occur in association with administration of injectable vaccines, including MRESVIA. Procedures should be in place to avoid injury from fainting.

5.3 Altered Immunocompetence

Immunocompromised individuals, including those receiving immunosuppressive therapy, may have a diminished immune response to MRESVIA.

6 ADVERSE REACTIONS

In a clinical trial conducted in participants 60 years of age and older, the most commonly reported (≥10%) adverse reactions were injection‑site pain (55.9%), fatigue (30.8%), headache (26.7%), myalgia (25.6%), arthralgia (21.7%), axillary (underarm) swelling or tenderness (15.2%), and chills (11.6%).

In a clinical trial conducted in participants 18 through 59 years of age at increased risk for LRTD caused by RSV, the most commonly reported (≥10%) adverse reactions were injection site pain (73.9%), fatigue (36.9%), headache (33.3%), myalgia (28.9%), arthralgia (22.7%), chills (19.9%), axillary (underarm) swelling or tenderness (17.1%), and nausea/vomiting (10.8%).

6.1 Clinical Trials Experience

Because clinical trials are conducted under widely varying conditions, adverse reaction rates observed in the clinical trials of a vaccine cannot be directly compared to rates in the clinical trials of another vaccine and may not reflect the rates observed in practice.

Individuals 60 Years of Age and Older

The safety of MRESVIA was evaluated in Study 1 (NCT05127434), a placebo-controlled, observer blinded clinical study conducted in 22 countries that includes participants from North America/ Europe, Central/Latin America, Africa and Asian/Pacific regions. A total of 18,231 participants received MRESVIA and 18,181 received saline placebo (0.5 mL).

In Study 1, the median age of the participants was 67 years (range 60‑108 years). Overall, 51.0% of the participants were male, 49.0% were female, 33.6% were Hispanic or Latino, 61.8% were White, 12.0% were Black or African American, 11.0% were Asian, 4.9% were American Indian or Alaska Native, 0.1% were Native Hawaiian or Pacific Islander, 5.5% were other races, and 4.1% were Multiracial.

Demographic characteristics were comparable between participants who received MRESVIA and those who received placebo.

Solicited Adverse Reactions: Local and systemic adverse reactions (ARs) were solicited in an electronic diary (eDiary) for 7 days following injection (i.e., the day of injection and 6 subsequent days) among participants receiving MRESVIA (n=18,160) and participants receiving placebo (n=18,098). Events that persisted for more than 7 days were followed until resolution, but not to exceed 28 days after the study injection.

The percentage of participants who reported solicited local and systemic adverse reactions are presented in Table 2 and Table 3. Solicited local and systemic adverse reactions had a median duration of 1 to 2 days.

Table 2: Percentage of Participants with Solicited Local Adverse Reactions Any Grade and ≥Grade 3 Starting Within 7 Days* of Vaccination
Local Adverse Reactions‡ | MRESVIA (N=18,154 – 18,156) % | Placebo† (N=18,093 – 18,094) %
Injection Site Pain, Any Grade§ | 55.9 | 13.8
Injection Site Pain, Grade 3§ | 1.7 | 1.1
Erythema (Redness), ≥ 2.5 cm | 2.0 | 0.6
Erythema (Redness), Grade 3, >10 cm | 0.6 | 0.3
Swelling (Hardness), ≥ 2.5 cm | 3.7 | 0.3
Swelling (Hardness), Grade 3, >10 cm | 0.9 | <0.1
Axillary (underarm) swelling or tenderness, Any Grade¶ | 15.2 | 6.1
Axillary (underarm) swelling or tenderness, Grade 3¶ | 0.8 | 0.6
Abbreviations: Any = Grade 1 or above; Percentages were based on the number of exposed participants who submitted any data for the event.
N = number of vaccinated participants with available data for the events listed.
* 7 days included day of vaccination and the subsequent 6 days. Adverse reactions and use of pain medication were collected in the electronic diary (e-diary).
† Placebo is 0.9% sodium chloride (normal saline) injection.
‡ No Grade 4 solicited local adverse reactions were reported.
§ Injection site pain grading scale: Does not interfere with activity (Grade 1); repeated use of over-the-counter pain reliever >24 hours or interferes with activity (Grade 2); any use of prescription pain reliever or prevents daily activity (Grade 3).
¶ Axillary (underarm) swelling or tenderness grading scale: No interference with activity (Grade 1); repeated use of over-the-counter pain reliever >24 hours or some interference with activity (Grade 2); any use of prescription pain reliever or prevents daily activity (Grade 3).

Table 3: Percentage of Participants with Solicited Systemic Adverse Reactions Any Grade and ≥Grade 3 Starting Within 7 Days* of Vaccination
Systemic Adverse Reactions‡ | MRESVIA (N=18,146 – 18,153) % | Placebo† (N=18,092 – 18,093) %
Fever, Any Grade (≥38°C / ≥100.4°F) | 2.7 | 1.3
Fever, Grade 3 (39.0°C – 40.0°C /; 102.1°F – 104.0°F) | 0.4 | 0.2
Fever, Grade 4 (>40.0°C / >104.0°F) | 0.2 | 0.2
Headache, Any Grade§ | 26.7 | 18.8
Headache, Grade 3§ | 1.5 | 1.1
Fatigue, Any Grade¶ | 30.8 | 20.0
Fatigue, Grade 3¶ | 1.7 | 1.2
Myalgia, Any Grade# | 25.6 | 14.4
Myalgia, Grade 3# | 1.4 | 0.8
Arthralgia, Any Grade# | 21.7 | 14.0
Arthralgia, Grade 3# | 1.1 | 0.7
Nausea/vomiting, Any Grade♠ | 7.0 | 5.2
Nausea/vomiting, Grade 3♠ | 0.4 | 0.4
Chills, Any Grade♥ | 11.6 | 6.8
Chills, Grade 3♥ | 0.6 | 0.4
Abbreviations: Any = Grade 1 or above; Percentages were based on the number of exposed participants who submitted any data for the event.
N = number of vaccinated participants with available data for the events listed.
* 7 days included day of vaccination and the subsequent 6 days. Adverse reactions and use of pain medication were collected in the electronic diary (e-diary).
† Placebo is 0.9% sodium chloride (normal saline) injection.
‡ With the exception of fever, no Grade 4 solicited systemic adverse reactions were reported.
§ Headache grading scale: No interference with activity (Grade 1); repeated use of over-the-counter pain reliever >24 hours or some interference with activity (Grade 2); significant, any use of prescription pain reliever or prevents daily activity (Grade 3).
¶ Fatigue grading scale: No interference with activity (Grade 1); some interference with activity (Grade 2); significant, prevents daily activity (Grade 3).
# Myalgia and arthralgia grading scales: No interference with activity (Grade 1); some interference with activity (Grade 2); significant, prevents daily activity (Grade 3).
♠ Nausea/vomiting grading scale: No interference with activity or 1-2 episodes per 24 hours (Grade 1); some interference with activity or >2 episodes per 24 hours (Grade 2); prevents daily activity, requires outpatient intravenous hydration (Grade 3).
♥ Chills grading scale: No interference with activity (Grade 1); some interference with activity not requiring medical intervention (Grade 2); prevents daily activity and requires medical intervention (Grade 3).

Unsolicited Adverse Events: Incidence of unsolicited adverse events, serious adverse events, and medically attended adverse events within 28 days of vaccination were similar in the groups that received MRESVIA or placebo. Unsolicited adverse events within 28 days considered related to the study vaccination were numerically higher in the recipients of MRESVIA (5.7%) than in the placebo recipients (4.4%), primarily attributed to events that were consistent with solicited adverse reactions.

There was a numerically higher incidence of urticaria in the MRESVIA group than the placebo group within 7 days post injection (8 and 2 participants, respectively) and within 28 days post injection (15 and 5 participants, respectively).

Serious Adverse Events: The median duration of safety follow-up was 311 days (range 1 to 585 days), and 96.6% of participants had at least a 6-month follow-up duration after vaccination. SAEs throughout the study were reported by 7.8% and 7.9% of participants in the MRESVIA group and the placebo group, respectively. One participant in the MRESVIA group had an SAE of facial paralysis with onset four days after vaccination assessed as related to MRESVIA. Within 28 days and 42 days post vaccination, there was no imbalance in reports of facial paralysis (including Bell’s palsy) between treatment groups. There were no other notable patterns or numerical imbalances between treatment groups for specific categories of serious adverse events that would suggest a causal relationship to MRESVIA.

Individuals 18 through 59 Years of Age at Increased Risk for LRTD Caused by RSV

The safety of MRESVIA was evaluated in Study 2 (NCT06067230) in which 502 participants aged 18 through 59 years at increased risk for LRTD caused by RSV received MRESVIA. Study 2 was conducted in the US, Canada and the United Kingdom.

From the day of vaccination (Day 1) through data cutoff for the safety analysis, the median duration of follow-up was 253 days (range: 8 to 349 days) in the MRESVIA group. As of the data cutoff date, 492/502 (98.0%) participants had completed at least 180 days of post-injection follow-up.

In Study 2, the median age of the participants in the MRESVIA group was 53.0 years (range 19‑59 years). Overall, 46.4% of the participants were male, 53.6% were female, 27.9% were Hispanic or Latino, 79.9% were White, 16.9% were Black or African American, 0.8% were Asian, 0.4% were American Indian or Alaska Native, 0.6% were Native Hawaiian or Pacific Islander, and 0.8% were Multiracial.

Conditions increasing the risk for RSV-LRTD were reported by the following percentages of participants in the MRESVIA group (individual participants may have reported more than 1 condition): diabetes mellitus (DM) in 59.6%, asthma in 38.8%, coronary artery disease (CAD) in 20.7%, chronic obstructive pulmonary disease (COPD) in 10.4%, congestive heart failure (CHF) in 9.0%, and chronic respiratory disease other than COPD or asthma in 2.4% of participants.

Solicited Adverse Reactions: Reactogenicity was assessed using a prespecified list of local and systemic adverse reaction terms that were actively solicited daily via eDiaries during the 7 days following vaccination (i.e., the day of vaccination and 6 subsequent days). The reported frequencies of specific solicited local and systemic adverse reactions among participants 18 through 59 years of age at increased risk for LRTD caused by RSV who received MRESVIA are presented in Table 4 and Table 5. Solicited local and systemic adverse reactions had a median onset of 2.0 days after vaccination and a median duration of 3 days.

Table 4: Percentage of Participants with Solicited Local Adverse Reactions Any Grade and ≥Grade 3 Starting Within 7 Days* of Vaccination with MRESVIA, Study 2
Local Adverse Reactions | (N=502) %
Injection Site Pain, Any Grade† | 73.9
Injection Site Pain, Grade 3 or Grade 4†, ‡ | 1.6
Erythema (Redness), ≥ 2.5 cm§ | 2.4
Erythema (Redness), Grade 3, > 10 cm§ | 0.0
Swelling (Hardness), ≥ 2.5 cm¶ | 4.6
Swelling (Hardness), Grade 3, >10 cm¶ | 0.2
Axillary (underarm) swelling or tenderness, Any Grade# | 17.1
Axillary (underarm) swelling or tenderness, Grade 3# | 0.6
Abbreviations: Any = Grade 1 or above; Percentages were based on the number of exposed participants who submitted any data for the event.
N = number of vaccinated participants with available data for the events listed.
* 7 days included day of vaccination and the subsequent 6 days. Adverse reactions and use of pain medication were collected in the electronic diary (e‑diary).
† Injection site pain grading scale: Does not interfere with activity (Grade 1); repeated use of over-the-counter pain reliever >24 hours or interferes with activity (Grade 2); any use of prescription pain reliever or prevents daily activity (Grade 3); requires emergency room visit or hospitalization (Grade 4).
‡ A single solicited local AR of injection site pain in the left arm was classified as Grade 4 on Day 3 due to an emergency room visit to rule out a cardiac event. The injection site pain resolved without treatment on Day 4.
§ Erythema grading scale: 25 to 50 mm / 2.5 to 5 cm (Grade 1); 51 to 100 mm / 5.1 to 10 cm (Grade 2); >100 mm / >10 cm (Grade 3); necrosis or exfoliative dermatitis (Grade 4). There were no Grade 4 solicited local ARs for erythema.
¶ There were no Grade 4 solicited local ARs for swelling.
# Axillary (underarm) swelling or tenderness grading scale: No interference with activity (Grade 1); repeated use of over-the-counter pain reliever >24 hours or some interference with activity (Grade 2); any use of prescription pain reliever or prevents daily activity (Grade 3). There were no Grade 4 solicited local ARs for axillary swelling or tenderness.

Table 5: Percentage of Participants with Solicited Systemic Adverse Reactions Any Grade and ≥Grade 3 Starting Within 7 Days* of Vaccination with MRESVIA, Study 2
Systemic Adverse Reactions | (N=502) %
Fever, Any Grade (≥38°C / ≥100.4°F)† | 3.6
Fever, Grade 3 (39.0°C – 40.0°C / 102.1°F – 104.0°F)† | 0.6
Headache, Any Grade‡ | 33.3
Headache, Grade 3‡ | 1.6
Fatigue, Any Grade§ | 36.9
Fatigue, Grade 3§ | 2.8
Myalgia, Any Grade¶ | 28.9
Myalgia, Grade 3¶ | 2.2
Arthralgia, Any Grade¶ | 22.7
Arthralgia, Grade 3¶ | 2.0
Nausea/vomiting, Any Grade# | 10.8
Chills, Any Grade♠ | 19.9
Chills, Grade 3♠ | 0.8
Abbreviations: Any = Grade 1 or above; Percentages were based on the number of exposed participants who submitted any data for the event.
N = number of vaccinated participants with available data for the events listed.
* 7 days included day of vaccination and the subsequent 6 days. Adverse reactions and use of pain medication were collected in the electronic diary (e‑diary).
† Fever grading scale: 38.0 to 38.4°C / 100.4 to 101.1°F (Grade 1); 38.5 to 38.9°C / 101.2 to 102.0°F (Grade 2); 39.0 to 40.0°C / 102.1 to 104.0°F (Grade 3); >40.0°C / >104.0°F (Grade 4)
‡ Headache grading scale: No interference with activity (Grade 1); repeated use of over-the-counter pain reliever >24 hours or some interference with activity (Grade 2); significant, any use of prescription pain reliever or prevents daily activity (Grade 3). No Grade 4 solicited systemic ARs were reported.
§ Fatigue grading scale: No interference with activity (Grade 1); some interference with activity (Grade 2); significant, prevents daily activity (Grade 3).
¶ Myalgia and arthralgia grading scales: No interference with activity (Grade 1); some interference with activity (Grade 2); significant, prevents daily activity (Grade 3).
# Nausea/vomiting grading scale: No interference with activity or 1-2 episodes per 24 hours (Grade 1); some interference with activity or >2 episodes per 24 hours (Grade 2); prevents daily activity, requires outpatient intravenous hydration (Grade 3).
♠ Chills grading scale: No interference with activity (Grade 1); some interference with activity not requiring medical intervention (Grade 2); prevents daily activity and requires medical intervention (Grade 3).

Serious Adverse Events: Overall, by the data cutoff, serious adverse events were reported for 19 participants (3.8%) in Study 2. No SAEs were assessed as related to MRESVIA.

8 USE IN SPECIFIC POPULATIONS

8.1 Pregnancy

Risk Summary

All pregnancies have a risk of birth defect, loss, or other adverse outcomes. In the U.S. general population, the estimated background risk of major birth defects and miscarriage in clinically recognized pregnancies is 2% to 4% and 15% to 20%, respectively.

There are no human data to establish whether there is a vaccine-associated risk with use of MRESVIA in pregnancy.

A developmental toxicity study was performed in female rats administered a vaccine formulation that included approximately twice the amount of nucleoside-modified messenger ribonucleic acid (mRNA), encoding the same RSV fusion (F) glycoprotein stabilized in the prefusion conformation, as in MRESVIA. The vaccine formulation was administered twice prior to mating and twice during gestation. The study revealed no evidence of harm to the fetus due to the vaccine (see Data).

Data

Animal Data

In a developmental toxicity study, 0.2 mL of a vaccine formulation containing 96 mcg of nucleoside‑modified mRNA per dose (a full human dose of MRESVIA contains 50 mcg of nucleoside‑modified mRNA) was administered to female rats by the intramuscular route on four occasions: 28 and 14 days prior to mating, and on gestation days 1 and 13. No vaccine‑related fetal malformations or variations and no adverse effects on postnatal development were observed in the study. The developmental toxicity study revealed no evidence of impaired female fertility.

8.2 Lactation

Risk Summary

It is not known whether MRESVIA is excreted in human milk. No human or animal data are available to assess the effects of MRESVIA on the breastfed infant or on milk production/excretion.

The developmental and health benefits of breastfeeding should be considered along with the mother’s clinical need for MRESVIA and any potential adverse effects on the breastfed child from MRESVIA or from the underlying maternal condition. For preventive vaccines, the underlying condition is susceptibility to disease prevented by the vaccine.

8.4 Pediatric Use

Safety and effectiveness of MRESVIA in individuals younger than 18 years of age have not been established.

8.5 Geriatric Use

Of the total number of participants (N = 36,412) who received MRESVIA or placebo in Study 1 (NCT05127434), 22,554 (61.9%) were 60 to 69 years of age, 10,972 (30.1%) were 70 to 79 years of age, and 2,886 (7.9%) were 80 years of age and older [see Adverse Reactions (6.1) and Clinical Studies (14)].

11 DESCRIPTION

MRESVIA is a sterile white to off-‑white injectable suspension for intramuscular use.

Each 0.5 mL dose of MRESVIA contains 50 mcg of nucleoside modified mRNA encoding the F glycoprotein from RSV subtype A stabilized in the prefusion conformation (pre-F protein).

Each 0.5 mL dose of MRESVIA also contains the following ingredients: a total lipid content of 1.02 mg (SM-102 (heptadecan-9-yl 8-((2-hydroxyethyl) (6-oxo-6-(undecyloxy) hexyl) amino) octanoate), polyethylene glycol 2000 dimyristoyl glycerol [PEG2000-DMG], cholesterol, and 1,2-distearoyl-sn-glycero-3-phosphocholine [DSPC]), 0.25 mg tromethamine, 1.2 mg tromethamine hydrochloride, 0.021 mg acetic acid, 0.10 mg sodium acetate trihydrate, 44 mg sucrose, and water for injection.

MRESVIA does not contain a preservative. The rubber tip cap and plunger used for the pre-filled syringe are not made with natural rubber latex.

12 CLINICAL PHARMACOLOGY

12.1 Mechanism of Action

MRESVIA induces an immune response against RSV pre-F protein that protects against LRTD caused by RSV.

13 NONCLINICAL TOXICOLOGY

13.1 Carcinogenesis, Mutagenesis, Impairment of Fertility

MRESVIA has not been evaluated for carcinogenic or mutagenic potential, or impairment of male fertility in animals.

14 CLINICAL STUDIES

14.1 Efficacy in Participants 60 Years of Age and Older

Study 1 (NCT05127434) is a randomized, placebo‑controlled, observer‑blind, case‑driven clinical study to evaluate the safety and efficacy of MRESVIA to prevent RSV‑LRTD in individuals 60 years of age and older with or without underlying medical conditions after receipt of a single dose of MRESVIA. Study 1 is being conducted in 22 countries and includes participants from North America/ Europe, Central/Latin America, Africa, and Asian/Pacific regions and is designed to follow participants for up to 24 months after vaccination.

Participants were randomized to a single dose of MRESVIA or placebo (in a 1:1 ratio). Randomization was stratified by age (60 to 74 years; ≥75 years) and risk factors for LRTD, which were defined as congestive heart failure (CHF) and/or chronic obstructive pulmonary disease (COPD) at screening.

The primary efficacy analysis population [Per‑Protocol (PP) Efficacy Set] included 35,064 participants who received either MRESVIA (n=17,561) or placebo (n=17,503), with a data cutoff of 30 Nov 2022. This study population included 49.1% female, 50.9% male, 63.4% White, 12.2% Black or African American, 8.7% Asian, 5.1% American Indian or Alaska Native, and 10.6% other. Among participants, 34.7% identified as Hispanic or Latino. The median age of participants was 67 years (range 60‑96 years), with 30.9% of participants between 70 and 79 years and 5.6% of participants ≥80 years. There were no notable differences in demographics or pre‑existing medical conditions between participants who received MRESVIA and those who received placebo. A total of 7.0% had protocol-defined LRTD risk factors (CHF and/or COPD) and 29.5% had one or more comorbidity of interest (COPD, asthma, chronic respiratory disease, diabetes, CHF, advanced liver disease, or advanced renal disease).

Study exclusion criteria included history of myocarditis, pericarditis, or myopericarditis within 2 months prior to screening; autoimmune conditions requiring systemic immunosuppressants (stable HIV‑positive participants were permitted); history of serious reaction to any prior vaccination. Individuals were not eligible for inclusion in the Per-Protocol Efficacy Set if they received any other vaccine within 28 days before or after administration of the study injection.

The primary efficacy endpoints were the prevention of a first episode of RSV‑LRTD with either ≥2 signs/symptoms or ≥3 signs/symptoms starting 14 days after vaccination. RSV-LRTD was defined based on the following criteria: The participant must have had RT-PCR-confirmed RSV infection and experienced new or worsening of ≥2 (or ≥3) of the following signs/symptoms for at least 24 hours: shortness of breath, cough and/or fever (≥37.8°C [100.0°F]), wheezing and/or rales and/or rhonchi, sputum production, tachypnea (≥20 breaths per minute or increase of ≥2 breaths per minute from baseline measurement in those who have baseline tachypnea), hypoxemia (new oxygen saturation ≤93% or new or increasing use of supplemental oxygen), or pleuritic chest pain. If signs/symptoms could not be captured, radiologic evidence of pneumonia with RT-PCR-confirmed RSV infection was also counted as RSV-LRTD.

The primary efficacy analyses were performed when at least 50% of targeted RSV-LRTD cases had accrued [which occurred after a median of 3.7 months of follow-up (range 15 to 379 days) when 20.2% of participants had reached 6 months of follow-up]. Both primary efficacy analyses met the predefined success criterion (lower bound of the alpha-adjusted CI of the VE was >20%). Additional analyses of efficacy were performed after a median of 8.6 months of follow-up (range 15 to 530 days) when 94.2% of participants had reached 6 months of follow-up after vaccination and met the same success criterion (lower bound of the 95% CI of the VE was >20%). Analyses of efficacy for both timepoints are presented in Table 6.

Table 6: Efficacy of MRESVIA to Prevent First Episode of Protocol‑Defined RSV-LRTD (Per‑Protocol Efficacy Set)
Primary Analyses; 3.7 months median follow-up | MRESVIA; (N=17,561); n (%) | Placebo; (N=17,503); n (%) | Vaccine Efficacy* Based on Hazard Ratio (%); (% CI†)
RSV-LRTD With 2 or More Signs/Symptoms | 15 (0.09) | 70 (0.40) | 78.7; (62.8, 87.9)
RSV-LRTD With 3 or More Signs/Symptoms | 5 (0.03) | 26 (0.15) | 80.9; (50.1, 92.7)
Additional Analyses; 8.6 months median follow-up | MRESVIA; (N=18,074); n (%) | Placebo; (N=18,010); n (%) | Vaccine Efficacy* Based on Hazard Ratio (%); (% CI‡)
RSV-LRTD With 2 or More Signs/Symptoms | 48 (0.27) | 127 (0.71) | 62.5; (47.7, 73.1)
RSV-LRTD With 3 or More Signs/Symptoms | 20 (0.11) | 51 (0.28) | 61.1 (34.7, 76.8)
Abbreviations: RSV-LRTD = Respiratory Syncytial Virus-Lower Respiratory Tract Disease; N = number of participants in Per-Protocol Efficacy set; n = number of participants with protocol defined RSV-LRTD; CI = Confidence Interval.
* Vaccine efficacy (VE) is defined as 100% x (1 - hazard ratio (MRESVIA vs. placebo)). The CI for VE is based on a stratified Cox proportional hazard model with Efron's method of tie handling and with the treatment group as a fixed effect, adjusting for stratification factors at randomization. Stratification factors at randomization are Age Group (60 to 74 years or 75 years and older) and LRTD Risk (Present or Absent).
† For primary analysis for RSV-LRTD with 2 or more symptoms, 95.04% CI where the alpha value of 4.96% was derived from the Lan-DeMets approximation to the Pocock stopping boundary with an information fraction of 0.99 (85 out of total of 86 cases). For primary analysis for RSV-LRTD with 3 or more symptoms, 95.10% CI where the alpha value of 4.90% was derived from the Lan-DeMets approximation to the Pocock stopping boundary with an information fraction of 0.97 (31 out of total of 32 cases).
‡ For additional analyses for RSV-LRTD with 2 or more and 3 or more symptoms, 95% CI.

Descriptive vaccine efficacy analyses by age subgroup and for participants with at least one comorbidity are presented in Table 7.

Table 7: Efficacy of MRESVIA to Prevent First Episode of RSV-LRTD With 2 or More Signs/Symptoms by Subgroup (8.6 Months Median Follow-up, Per‑Protocol Efficacy Set)
Subgroup | MRESVIA; Cases, n/N† | Placebo Cases, n/N† | VE*, % (95% CI)
Overall (≥60 years) | 48/18,074 | 127/18,010 | 62.5 (47.7, 73.1)
60 to 69 years | 32/11,193 | 77/11,146 | 58.8 (37.8, 72.7)
70 to 79 years | 10/5,455 | 45/5,431 | 78.0 (56.3, 88.9)
≥80 years | 6/1,426 | 5/1,433 | -20.0 (-293.3, 63.4)‡
≥60 years with ≥1 comorbidity§ | 17/5,365 | 51/5,244 | 67.4 (43.6, 81.2)
Abbreviations: RSV-LRTD = Respiratory Syncytial Virus-associated Lower Respiratory Tract Disease
* Vaccine efficacy (VE) is defined as 100% x (1 - hazard ratio (MRESVIA vs. placebo)). The CI for VE is based on a stratified Cox proportional hazard model with Efron's method of tie handling and with the treatment group as a fixed effect, adjusting for stratification factors at randomization. All the VE analyses presented are descriptive.
† Based on the number of participants in each subgroup.
‡ VE cannot be reliably estimated due to the low number of cases accrued in this age group.
§ Comorbidities included in this analysis were chronic cardiopulmonary conditions, including CHF, COPD, asthma and chronic respiratory conditions as well as diabetes, advanced liver, and advanced kidney disease.

14.2 Immunogenicity in Participants 18 through 59 Years of Age at Increased Risk for LRTD Caused by RSV

Study 2 evaluated the immunogenicity of MRESVIA in adults aged 18 through 59 years at increased risk for LRTD caused by RSV. Participants had documented confirmation of at least one of the following conditions: CAD and/or CHF, chronic lung disease (including but not limited to COPD or persistent asthma), and Type 1 or Type 2 DM. The demographic characteristics of participants in the Per-Protocol (PP) set in Study 2 were similar to those of the Safety Set. Effectiveness of MRESVIA in this population was assessed by comparison of neutralizing antibody (nAb) levels against the two major RSV subtypes, RSV-A and RSV-B, at Day 29 post-vaccination to those in a subset of Study 1 participants ≥60 years of age. The percentage of Study 1 subset participants who had at least one chronic medical condition (COPD, asthma, chronic respiratory disease, diabetes, CHF, advanced liver disease or advanced renal disease) was 57.2%.

In analyses of the primary endpoints, non-inferiority was demonstrated for the nAb Geometric Mean Titers (GMTs) for RSV-A and RSV-B [Study 2 PP/Study 1 Per-Protocol Immunogenicity (PPI) subset; lower bound of the 2‑sided 95% CIs of the Geometric Mean Ratio (GMR) > 0.667] (Table 8).

Table 8: Comparison of Model-Adjusted RSV Neutralizing GMTs at Day 29 after Vaccination with MRESVIA, 18 through 59 Years of Age at Increased Risk of LRTD Caused by RSV (Study 2) versus 60 Years of Age and Older (Study 1)
 | Study 2 18 through 59 years of age at increased risk of RSV-LRTD (PP Set) (N=489-492) | Study 1 ≥ 60 years of age (PPI Set) (N=1511-1513) | Study 2 versus Study 1
RSV subgroups | GMTa (95% CI) | GMTa (95% CI) | GMR 95% CI
RSV-A | 23245; (21326, 25336) | 19988; (19038, 20985) | 1.2; (1.1, 1.3)
RSV-B | 7831; (7242, 8467) | 6901; (6603, 7213) | 1.1; (1.0, 1.2)
PP=Per-Protocol
PPI=Per-Protocol Immunogenicity
GMT=Geometric Mean Titer
GMR=Geometric Mean Ratio
N = Number of participants with available antibody data at baseline (Day 1) and Day 29.
Antibody values reported as below the lower limit of quantification (LLOQ) are replaced by 0.5 x LLOQ. Values greater than the upper limit of quantification (ULOQ) are replaced by the ULOQ.
a The model-adjusted GMT is estimated on Analysis of covariance (ANCOVA) model. In the ANCOVA model, the log-transformed antibody levels at Day 29 post baseline are treated as a dependent variable, with the treatment group as an explanatory variable and the log-transformed baseline antibody level as a covariate. The resulted least square (LS) means, difference of LS means, and 95% CI are back transformed to the original scale for presentation.

Seroresponse Rate Difference between Study 2 and Study 1 for Day 29 nAb (RSV-A and RSV-B)

Seroresponse for RSV-A and RSV-B nAb is defined as a post-primary dose titer ≥ 4 × LLOQ if baseline is < LLOQ or a ≥ 4-fold increase from baseline if baseline is ≥ LLOQ. The difference in seroresponse rate (SRR) for RSV‑A was 11.8% (95% CI: 7.8, 15.5) and for RSV-B was 10.8% (95% CI: 5.9, 15.6). These differences met prespecified non-inferiority criteria (lower bound of the 95% CI > -10%). Study 2 SRR (95% CI) at Day 29 for RSV-A was 85.8% (82.4, 88.7) and for RSV-B was 67.3% (62.9, 71.4). Study 1 SRR (95% CI) at Day 29 for RSV‑A was 74.0% (71.7, 76.2) and for RSV-B was 56.5% (53.9, 59.0).

16 HOW SUPPLIED/STORAGE AND HANDLING

16.1 How Supplied

MRESVIA is supplied as follows:

NDC 80777‑345‑62 Carton of 1 single‑dose pre-filled syringe in a paperboard tray. The syringe contains 1 dose of 0.5 mL (NDC 80777-345-01).

NDC 80777‑345‑90 Carton of 1 single‑dose pre-filled syringe in a blister pack. The syringe contains 1 dose of 0.5 mL (NDC 80777-345-01).

NDC 80777-345-63 Carton of 2 single-dose pre-filled syringes in a paperboard tray; each syringe contains 1 dose of 0.5 mL (NDC 80777-345-01).

NDC 80777-345-89 Carton of 2 single-dose pre-filled syringes in a blister pack; each syringe contains 1 dose of 0.5 mL (NDC 80777-345-01). Each carton contains 1 blister, and each blister contains two syringes. Use one syringe per dose.

NDC 80777‑345‑61 Carton of 10 single‑dose pre-filled syringes in a paperboard tray; each syringe contains 1 dose of 0.5 mL (NDC 80777-345-01).

NDC 80777‑345‑96 Carton of 10 single‑dose pre-filled syringes in a blister pack; each syringe contains 1 dose of 0.5 mL (NDC 80777-345-01). Each carton contains 5 blister packs, and each blister pack contains two syringes. Use one syringe per dose..

16.2 Storage and Handling

During storage, minimize exposure to room light, and avoid exposure to direct sunlight and ultraviolet light.

Frozen Storage

Store frozen between -40°C to ‑15°C (-40°F to 5°F).

Storage after Thawing

Storage at 2°C to 8°C (36°F to 46°F):

- Pre-filled syringes may be stored refrigerated between 2°C to 8°C (36°F to 46°F) for up to 90 days prior to use.

Storage at 8°C to 25°C (46°F to 77°F):

- Pre-filled syringes may be stored between 8°C to 25°C (46°F to 77°F) for a total of 24 hours after removal from refrigerated conditions. Discard the pre-filled syringe if not used within this time. Syringes should not be returned to the refrigerator after being thawed at room temperature.
- Total storage at 8°C to 25°C (46°F to 77°F) must not exceed 24 hours.
- Do not refreeze once thawed. Do not shake.

Transportation of Thawed Pre-filled Syringes

Thawed pre-filled syringes can be transported at 2°C to 8°C (36°F to 46°F) using shipping containers which have been qualified to maintain 2°C to 8°C (36°F to 46°F). Once thawed and transported at 2°C to 8°C (36°F to 46°F), pre-filled syringes should not be refrozen and should be stored at 2°C to 8°C (36°F to 46°F) until use.

17 PATIENT COUNSELING INFORMATION

Advise the vaccine recipient or caregiver to read the FDA-approved patient labeling (INFORMATION FOR RECIPIENTS AND CAREGIVERS).

Prior to administration of MRESVIA:

- Inform vaccine recipient or caregiver of the potential benefits and risks of vaccination with MRESVIA.
- Instruct vaccine recipient or caregiver to report any adverse events to their healthcare provider or to the Vaccine Adverse Event Reporting System at 1-800-822-7967 and www.vaers.hhs.gov.

This product’s labeling may have been updated. For the most recent prescribing information, please visit modernatx.com/products/mresvia or mRESVIApro.com.

Manufactured for:
Moderna US, Inc.
5 Vaughn Drive
Princeton, NJ 08540

©2025 ModernaTX, Inc. All rights reserved.

MRESVIA is a trademark of ModernaTX, Inc.

Patent(s): www.modernatx.com/patents

Revised: 06/2025

INFORMATION FOR RECIPIENTS AND CAREGIVERS

MRESVIA (pronounced em res’ vee ah)

(Respiratory Syncytial Virus Vaccine)

Please read this information sheet before getting MRESVIA. This summary is not intended to take the place of talking with your healthcare provider. If you have questions or would like more information, please talk with your healthcare provider.

What is MRESVIA?

MRESVIA is a vaccine to protect you against lower respiratory tract disease caused by Respiratory Syncytial Virus (RSV).

MRESVIA is for people 60 years of age and older and also for people 18 through 59 years of age who are at increased risk for RSV (people with medical conditions such as diabetes or with diseases affecting the lungs and heart). Vaccination with MRESVIA may not protect all people who receive the vaccine.

MRESVIA does not contain RSV. MRESVIA cannot give you lower respiratory tract disease caused by RSV.

Who should not get MRESVIA?

You should not get MRESVIA if you had

- a severe allergic reaction to any ingredient in MRESVIA (see What are the ingredients in MRESVIA?)

What should I tell my healthcare provider?

Tell your healthcare provider about all of your medical conditions, including if you:

- have any allergies
- had a severe allergic reaction after receiving a previous dose of any other vaccine
- have a fever
- have a bleeding disorder or are on a blood thinner
- are immunocompromised or are on a medicine that affects your immune system
- have received any other RSV vaccine
- have ever fainted in association with an injection

How is MRESVIA given?

MRESVIA is given as an injection into the muscle.

What are the risks of MRESVIA?

There is a very small chance that MRESVIA could cause a severe allergic reaction. A severe allergic reaction would usually occur within a few minutes to one hour after getting a dose of MRESVIA. For this reason, your healthcare provider may ask you to stay for a short time at the place where you received your vaccine. Signs of a severe allergic reaction may include:

- Trouble breathing
- Swelling of your face and throat
- A fast heartbeat
- A rash all over your body
- Dizziness and weakness

Side effects that have been reported in clinical trials with MRESVIA include:

- Injection‑site reactions: pain, underarm swelling or tenderness in the same arm of the injection, swelling (hardness), and redness
- Fatigue, headache, muscle pain, joint pain, chills, nausea or vomiting, fever, hives, and facial paralysis

These may not be all of the possible side effects of MRESVIA. Ask your healthcare provider about any side effects that concern you. You may report side effects to the Vaccine Adverse Event Reporting System (VAERS) at 1-800-822-7967 or https://vaers.hhs.gov.

What are the ingredients in MRESVIA?

MRESVIA contains the following ingredients:

- messenger ribonucleic acid (mRNA)
- lipids (SM-102, polyethylene glycol dimyristoyl glycerol [PEG2000-DMG], cholesterol, and 1,2-distearoyl-sn-glycero-3-phosphocholine [DSPC])
- tromethamine
- tromethamine hydrochloride
- acetic acid
- sodium acetate trihydrate
- sucrose
- water

MRESVIA does not contain preservative.

What if I have additional questions?

If you would like more information, talk to your healthcare provider, or visit MRESVIA.com or call 1‑866‑MODERNA (1‑866‑663‑3762).

Manufactured for:
Moderna US, Inc.
5 Vaughn Drive
Princeton, NJ 08540

©2025 ModernaTX, Inc. All rights reserved.

MRESVIA is a trademark of ModernaTX, Inc.

Patent(s): www.modernatx.com/patents

Revised: 06/2025

Package/Label Display Panel

Respiratory Syncytial Virus Vaccine NDC 80777-345-01 0.5 mL Single Dose Rx Only For IM Use Mfd. for: Moderna US, Inc.

Package/Label Display Panel

NDC 80777-345-90 Respiratory Syncytial Virus Vaccine mRESVIATM Injectable Suspension For 60 years and older For intramuscular use

Package/Label Display Panel

NDC 80777-345-96 Respiratory Syncytial Virus Vaccine mRESVIATM Injectable Suspension For 60 years and older For intramuscular use

Package/Label Display Panel

NDC 80777-345-89 Respiratory Syncytial Virus Vaccine mRESVIATM Injectable Suspension For 60 years and older For intramuscular use

Package/Label Display Panel

NDC 80777-345-62 Respiratory Syncytial Virus Vaccine mRESVIATM Injectable Suspension For individuals 60 years and older For individuals 18 through 59 years at increased

risk for lower respiratory tract disease caused by RSV For intramuscular use

Package/Label Display Panel

NDC 80777-345-63 Respiratory Syncytial Virus Vaccine mRESVIATM Injectable Suspension For individuals 60 years and older For individuals 18 through 59 years at increased

risk for lower respiratory tract disease caused by RSV For intramuscular use

Package/Label Display Panel

NDC 80777-345-61 Respiratory Syncytial Virus Vaccine mRESVIATM Injectable Suspension For individuals 60 years and older For individuals 18 through 59 years at increased

risk for lower respiratory tract disease caused by RSV For intramuscular use